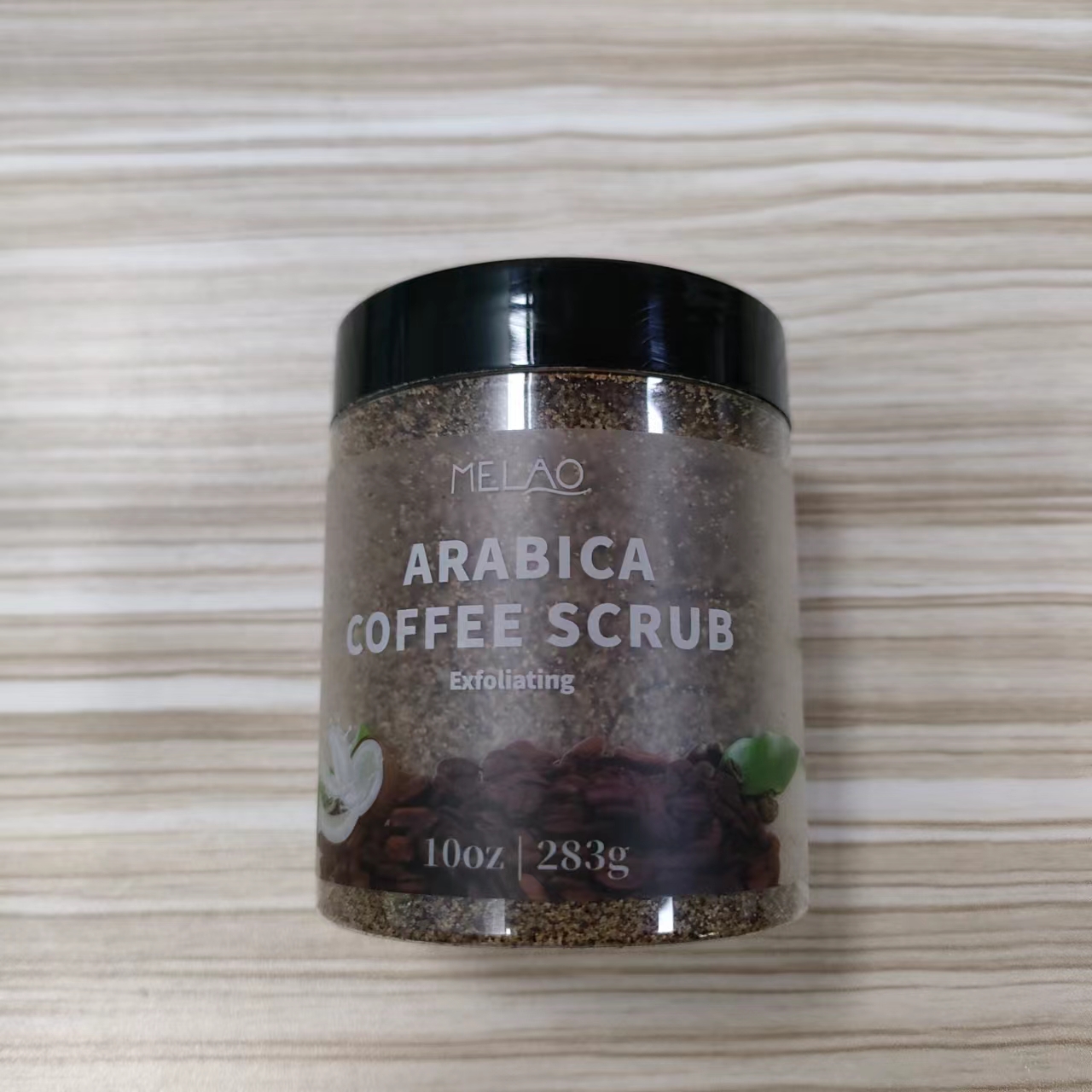 DRUG LABEL: MELAO ARABICA COFFEE SCRUB
NDC: 74458-232 | Form: GRANULE
Manufacturer: Guangzhou Yilong Cosmetics Co., Ltd
Category: otc | Type: HUMAN OTC DRUG LABEL
Date: 20241111

ACTIVE INGREDIENTS: COCOA 1 g/100 g; COFFEA ARABICA (COFFEE) SEED OIL 3 g/100 g; COCOS NUCIFERA (COCONUT) OIL 2 g/100 g
INACTIVE INGREDIENTS: COFFEA ARABICA (COFFEE) SEED EXTRACT; OLEA EUROPAEA (OLIVE) FRUIT OIL; PRUNUS AMYGDALUS DULCIS (SWEET ALMOND) OIL; BUTYROSPERMUM PARKII (SHEA) BUTTER; SODIUM CHLORIDE

MELAO ARABICA COFFEE SCRUB

ACTIVE INGREDIENT

Coffea Arabica (Coffee) Seed Oil

Cocos Nucifera (Coconut) Oil

Theobroma Cacao (Cocoa) Extract

INACTIVE INGREDIENT

Sodium Chloride

Coffea Arabica (Coffee) Seed Extract

Olea Europaea (Olive) Fruit Oil

Prunus Amygdalus Dulcis (Sweet Almond) Oil

Butyrospermum Parkii (Shea) Butter

PURPOSE

Exfoliating.

INDICATIONS AND USAGE

During the shower, take an appropriate amount of the scrub and apply it to the body, rubbing and circling for about 5 minutes, especially in the parts of the joints where there is more waste keratin, rubbing a few more times, and finally rinsing off with water. Once every two weeks is best.

DOSAGE AND ADMINISTRATION

During the shower, take an appropriate amount of the scrub and apply it to the body, rubbing and circling for about 5 minutes, especially in the parts of the joints where there is more waste keratin, rubbing a few more times, and finally rinsing off with water. Once every two weeks is best.

WARNINGS

For external use only.

Stop use and ask a doctor if rash occurs.

Do not use on damaged or broken skin.

When using this product keep out of eyes. Rinse with water to remove.

Keep out of reach of children. If swallowed, get medical help or contact a Poison Control Center right away.